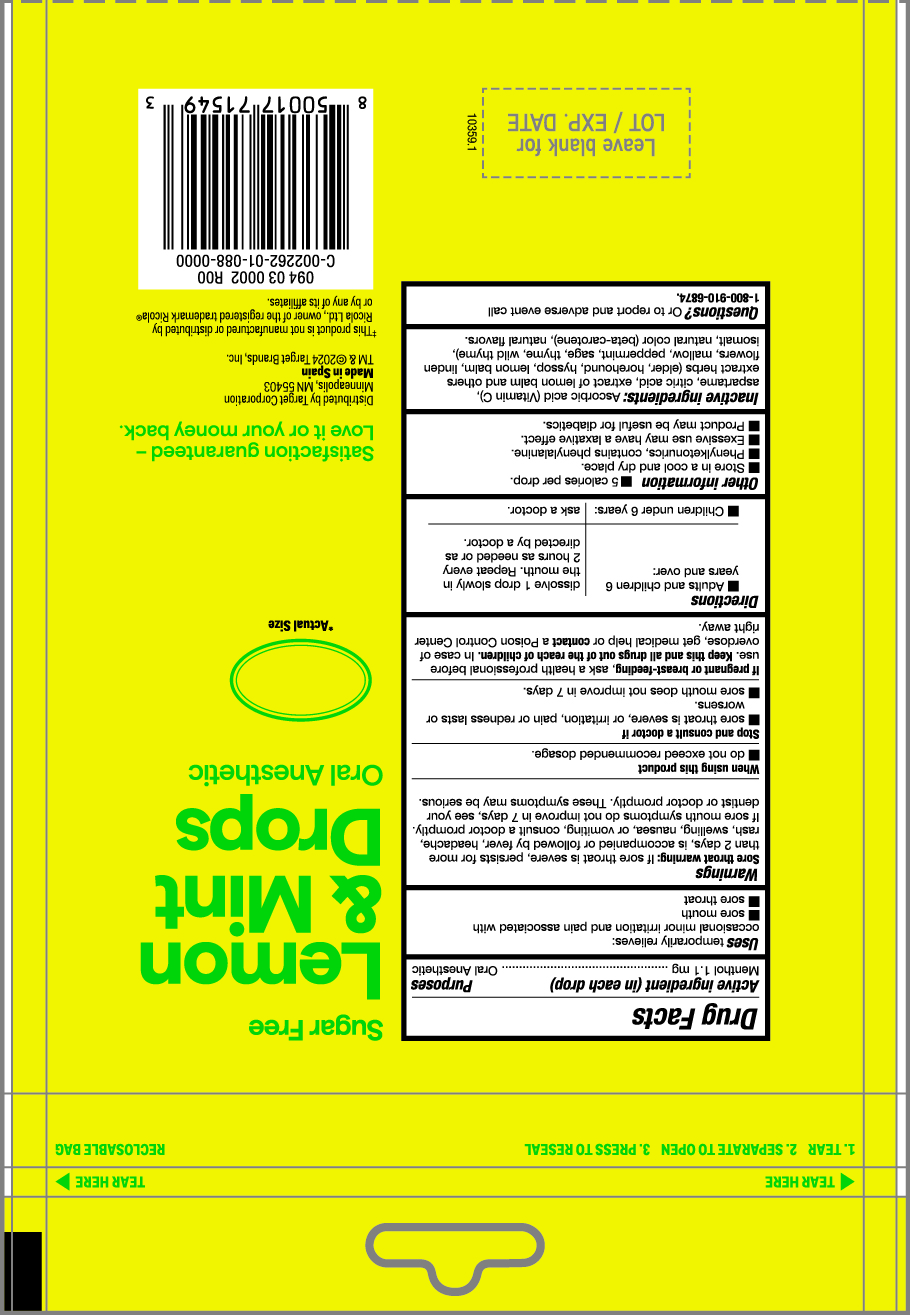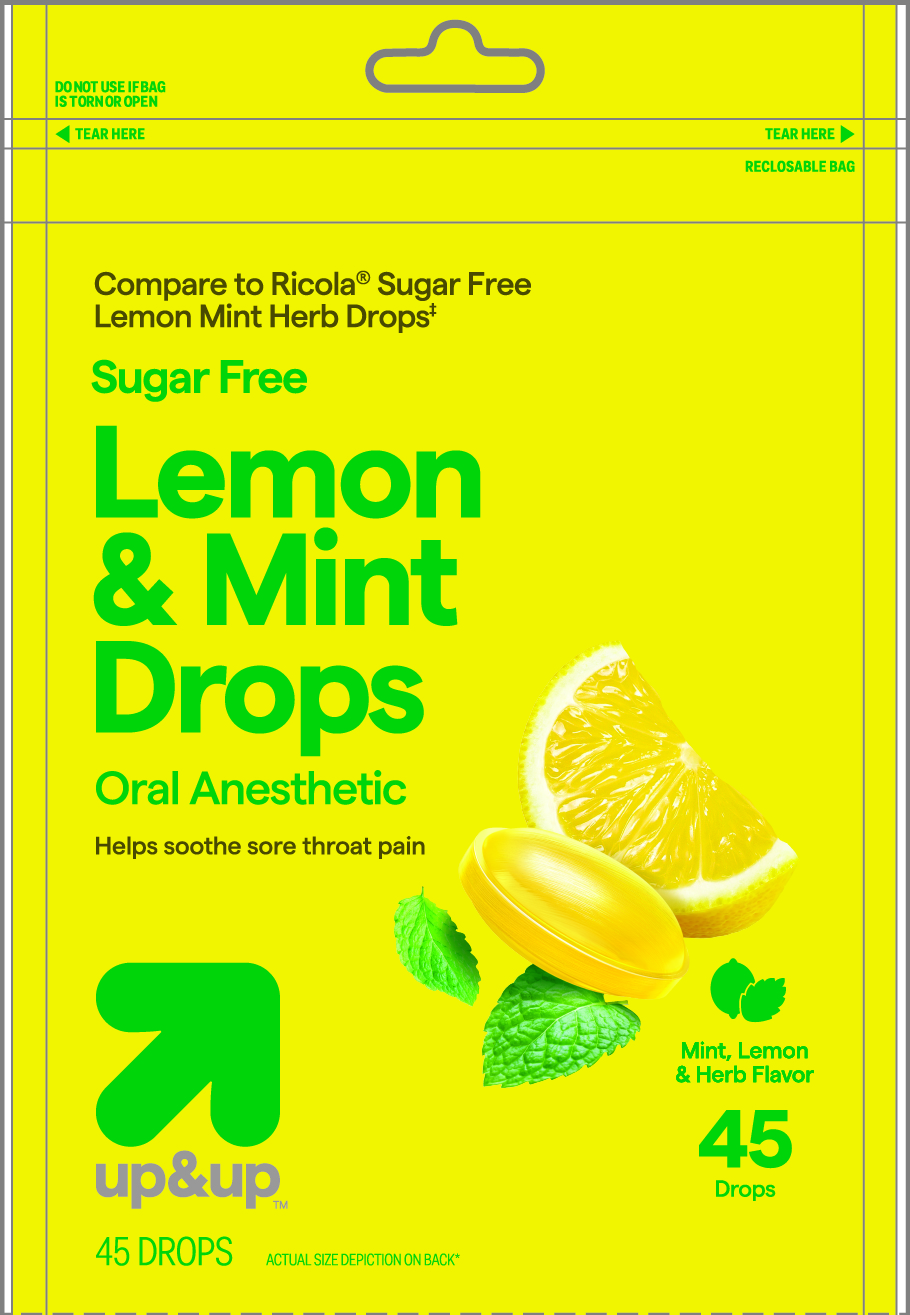 DRUG LABEL: Lemon Mint Drops
NDC: 82442-202 | Form: PASTILLE
Manufacturer: Target Corporation Inc.
Category: otc | Type: HUMAN OTC DRUG LABEL
Date: 20240514

ACTIVE INGREDIENTS: MENTHOL 1.1 mg/1 1
INACTIVE INGREDIENTS: FLAVONE; TILIA CORDATA FLOWER; ASCORBIC ACID; ASPARTAME; CITRIC ACID MONOHYDRATE; LEMON BALM OIL; SAMBUCUS NIGRA FLOWER; HOREHOUND; HYSSOPUS OFFICINALIS WHOLE; THYME; ISOMALT; MALVA SYLVESTRIS LEAF; PEPPERMINT; SAGE; BETA CAROTENE; WILD THYME

Lemon Mint Drops

Active ingredient Menthol 1.1 mg

Oral anesthetic

PURPOSE

Uses temporarily relieves:

ocasional minor irritation and pain associated with

- sore mouth
- sore throat

INDICATIONS AND USAGE

Uses temporarily relieves:

ocasional minor irritation and pain associated with

- sore mouth
- sore throat

Warnings

Sore throat warning: if sore throat is severe, persists for more than 2 days, is accompanied or followed by fever, headache, rash swelling, nausea or vomiting , consult a doctor promptly. If sore mouth symptons do not improve in 7 days, see your dentist or doctor promptly. These symptons may be serious .

Stop and consult a doctor if

- sore mouth does not improve in 7 days.
- sore throat is severe, or irritation, pain or redness lasts or worsens.

Stop and consult a doctor if

sore mouth does not improve in 7 days.
sore throat is severe, or irritation, pain or redness lasts or worsens.

PREGNANCY OR BREAST FEEDING

If pregnant or breast-feeding, ask a health professional before use.

KEEP OUT OF REACH OF CHILDREN

Keep this and all drugs out of the reach of children.

OVERDOSAGE

In case of accidental overdose, get medical help or contact a Poison Control Center right away.

Directions

- Adults and children 6 years and over: dissolve 1 drop slowly in mouth. Repeated every 2 hours as needed or as directed by a doctor.
- Children under 6 years: as a doctor

OTHER SAFETY INFORMATION

- 5 calories per dop
- Store in a cool and dry place
- Phenylketonurics, contains phenylalanine
- Excessive use may have a laxative effect.
- Product may be useful for diabetics

INACTIVE INGREDIENT

ascorbic acid (vitamin C), aspartame, citric acid, extract of lemon balm and others extract herbs (elder, horehound, hyssop, lemon balm, linden flowers, mallow, peppermint, sage, thyme, wild thyme),isomalt, natural color (beta-carotene), natural flavors.

QUESTIONS

Questions? or to report and adverse event call: 1-800-910-68-74